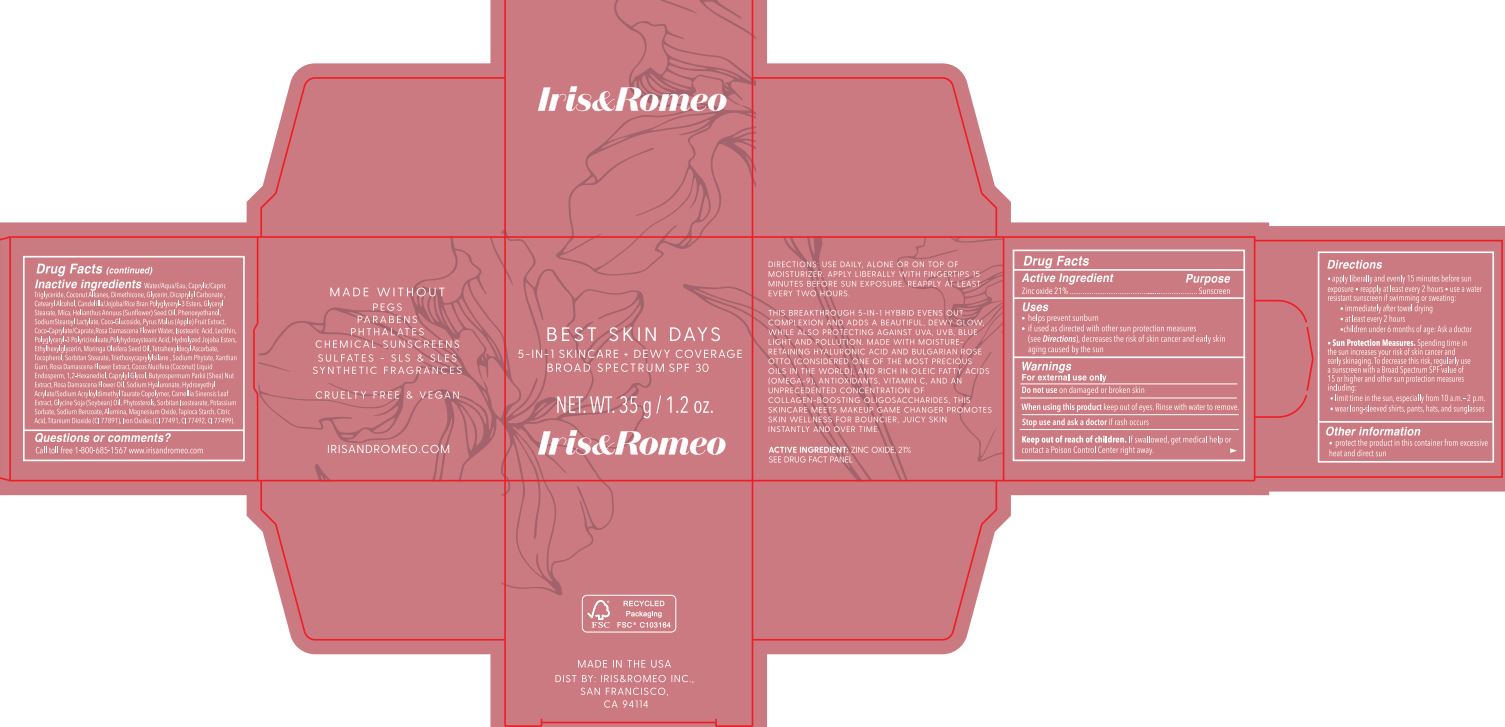 DRUG LABEL: Best Skin Days BS SPF 30
NDC: 62742-4243 | Form: CREAM
Manufacturer: Allure Labs
Category: otc | Type: HUMAN OTC DRUG LABEL
Date: 20231226

ACTIVE INGREDIENTS: ZINC OXIDE 21 g/100 g
INACTIVE INGREDIENTS: ROSA X DAMASCENA FLOWER OIL; GREEN TEA LEAF; SORBITAN ISOSTEARATE; ALUMINUM OXIDE; LECITHIN, SOYBEAN; SUNFLOWER OIL; TITANIUM DIOXIDE; FERRIC OXIDE RED; ISOSTEARIC ACID; ETHYLHEXYLGLYCERIN; PHYTATE SODIUM; GLYCERIN; CETOSTEARYL ALCOHOL; POLYGLYCERYL-3 LAURATE; WATER; DIMETHICONE; TETRAHEXYLDECYL ASCORBATE; SOYBEAN OIL; POLYHYDROXYSTEARIC ACID (2300 MW); ROSA DAMASCENA FLOWER; MEDIUM-CHAIN TRIGLYCERIDES; DICAPRYLYL CARBONATE; CANDELILLA WAX; JOJOBA OIL; POLYGLYCERYL-3 PENTARICINOLEATE; HYDROLYZED JOJOBA ESTERS (ACID FORM); XANTHAN GUM; RICE BRAN; MICA; SODIUM STEAROYL LACTYLATE; TOCOPHEROL; TRIETHOXYCAPRYLYLSILANE; COCONUT WATER; ENDOSPERMUM MOLUCCANUM WHOLE; HYDROXYETHYL ACRYLATE/SODIUM ACRYLOYLDIMETHYL TAURATE COPOLYMER (100000 MPA.S AT 1.5%); PHENOXYETHANOL; COCO GLUCOSIDE; COCO-CAPRYLATE/CAPRATE; MORINGA OLEIFERA SEED OIL; SORBITAN MONOSTEARATE; 1,2-HEXANEDIOL; CAPRYLYL GLYCOL; MAGNESIUM OXIDE; STARCH, TAPIOCA; CITRIC ACID MONOHYDRATE; PHYTOSTERYL MACADAMIATE; SODIUM BENZOATE; FERROSOFERRIC OXIDE; COCONUT ALKANES; GLYCERYL MONOSTEARATE; APPLE; SHEANUT; HYALURONATE SODIUM; POTASSIUM SORBATE; FERRIC OXIDE YELLOW

Drug Facts

Active Ingredient: Zinc Oxide - 21%

Purpose: Sunscreen

Uses:

Helps prevent sunburn.

If you used as directed with other sun protection measures (See Directions), decreases the risk of skin cancer and early skin aging caused by the sun.

Warning:

For external use only

Do not use on damaged or broken skin.

When using this product keep out of eyes. Rinse with water to remove.

Stop use and ask a doctor if rash occurs.

Keep out of reach of children. If swallowed, get medical help or contact a Poison Control Center right away.

DOSAGE AND ADMINISTRATION

Direction:

Apply liberally and evenly 15 minutes before sun exposure. reapply at least every 2 hours. Use a water resistant sunscreen if swimming or sweating: immediately after towel drying. At least every 2 hours. children under 6 months of age: Ask a doctor

Sun Protection Measures: Spending time in the sun increases your risk of skin cancer and early skin aging. To decrease this risk, regularly use a sunscreen with a Broad Spectrum SPF value of 15 or higher and other sun protection measures including: limit time in the sun, especially from 10 a.m. – 2 p.m., wear long sleeved shirts, pants, hats, and sunglasses.

Other information:

Protect the product in this container from excessive heat and direct sun.

Inactive ingredients:

Water /Aqua/Eau, Caprylic/Capric Triglyceride, Coconut Alkanes, Dimethicone, Glycerin, Dicaprylyl Carbonate, Cetearyl Alcohol, Candelilla/Jojoba/Rice Bran Polyglyceryl-3 Esters, Glyceryl Stearate, Mica, Helianthus Annuus (Sunflower) Seed Oil, Phenoxyethanol, Sodium Stearoyl Lactylate, Coco-Glucoside, Pyrus Malus (Apple) Fruit Extract, Coco-Caprylate/Caprate, Rosa Damascena Flower Water, Isostearic Acid, Lecithin, Polyglyceryl-3 Polyricinoleate, Polyhydroxystearic Acid, Hydrolyzed Jojoba Esters, Ethylhexylglycerin, Moringa Oleifera Seed Oil, Tetrahexyldecyl Ascorbate, Tocopherol, Sorbitan Stearate, Triethoxycaprylylsilane, Sodium Phytate, Xanthan Gum, Rosa Damascena Flower Extract, Cocos Nucifera (Coconut) Liquid, Endosperm, 1,2-Hexanediol, Caprylyl Glycol, Butyrospermum Parkii (Shea) Nut Extract, Rosa Damascena Flower Oil, Sodium Hyaluronate, Hydroxyethyl Acrylate/Sodium Acryloyldimethyl Taurate Copolymer, Camellia Sinensis Leaf Extract, Glycine Soja (Soybean) Oil, Phytosterols, Sorbitan Isostearate, Potassium Sorbate, Sodium Benozate, Alumina, Magnesium Oxide, Tapioca Starch, Citric Acid, Titanium Dioxide (CI 77891), Iron Oxides (CI 77491,CI77492,CI77499)